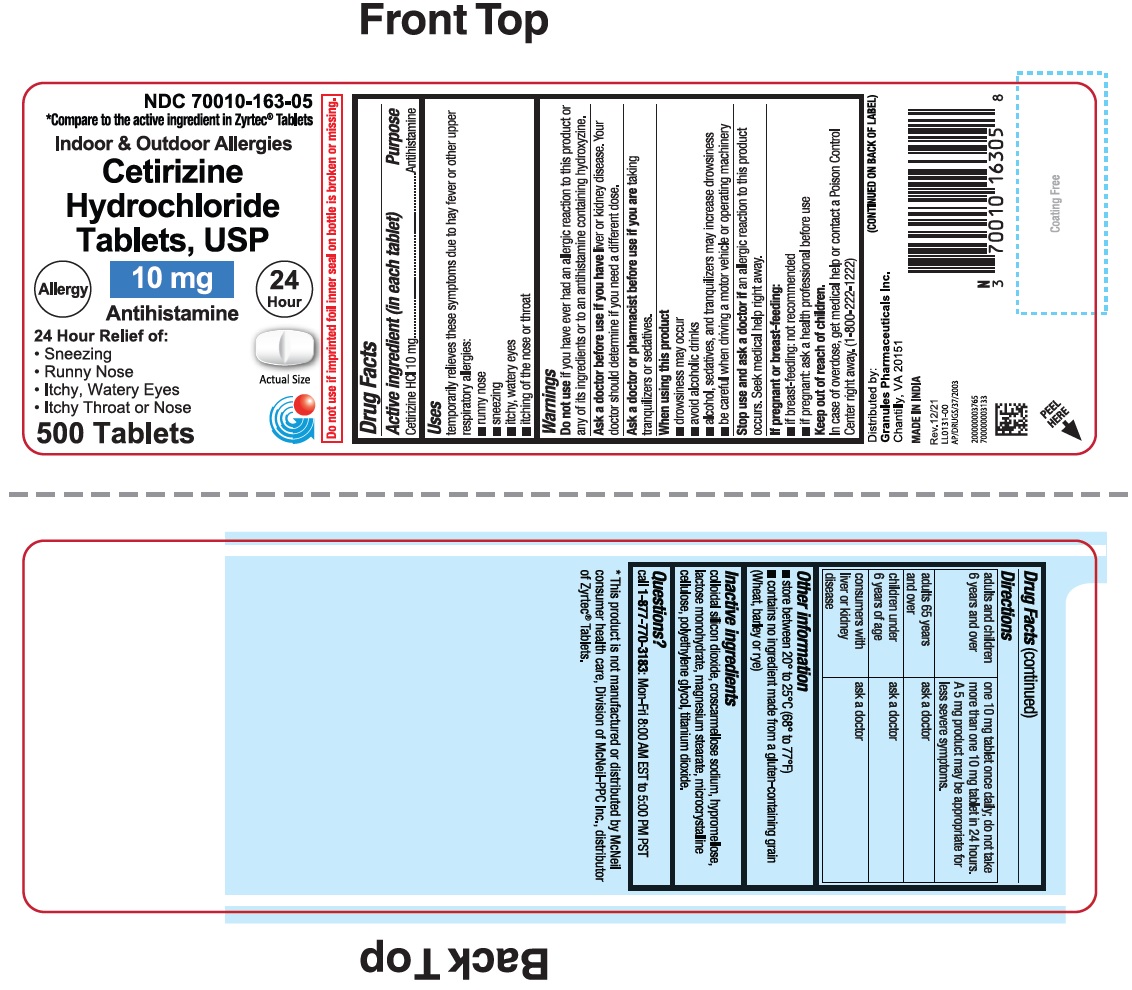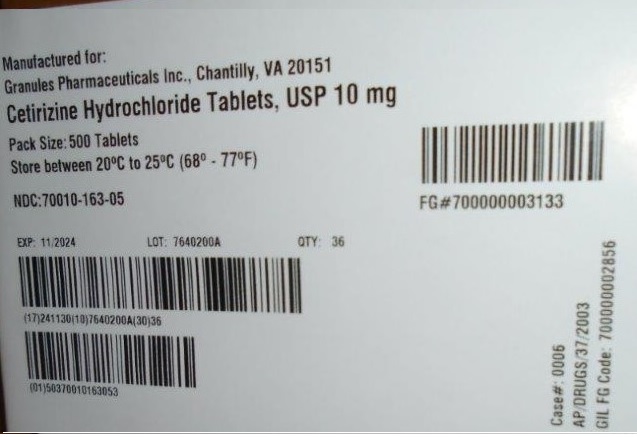 DRUG LABEL: Cetirizine hydrochloride
NDC: 70010-163 | Form: TABLET, COATED
Manufacturer: Granules Pharmaceuticals Inc.
Category: otc | Type: HUMAN OTC DRUG LABEL
Date: 20251204

ACTIVE INGREDIENTS: CETIRIZINE HYDROCHLORIDE 10 mg/1 1
INACTIVE INGREDIENTS: CROSCARMELLOSE SODIUM; SILICON DIOXIDE; MAGNESIUM STEARATE; CELLULOSE, MICROCRYSTALLINE; HYPROMELLOSE, UNSPECIFIED; TITANIUM DIOXIDE; POLYETHYLENE GLYCOL; LACTOSE MONOHYDRATE

Cetrizine Hydrochloride Tablets

Cetirizine Hydrochloride Tablets

Drug Facts

Active Ingredient

Cetirizine HCl 10 mg

PURPOSE

Antihistamine

USE(S)

temporarily relieves these symptoms due to hay fever or other upper respiratory allergies:

- runny nose
- sneezing
- itchy, watery eyes
- itching of the nose or throat

DO NOT USE

if you have ever had an allergic reaction to this product or any of its ingredients or to an antihistamine containing hydroxyzine.

ASK A DOCTOR BEFORE USE IF

liver or kidney disease. Your doctor should determine if you need a different dose.

ASK A DOCTOR OR PHARMACIST BEFORE USE IF

taking tranquilizers or sedatives.

WHEN USING THIS PRODUCT

- drowsiness may occur
- avoid alcoholic drinks
- alcohol, sedatives, and tranquilizers may increase drowsiness
- be careful when driving a motor vehicle or operating machinery

STOP USE AND ASK DOCTOR IF

an allergic reaction to this product occurs. Seek medical help right away.

PREGNANCY/BREASTFEEDING

- if breast-feeding: not recommended
- if pregnant: ask a health professional before use.

KEEP OUT OF REACH OF CHILDREN

In case of overdose, get medical help or contact a Poison Control Center right away. (1-800-222-1222)

DIRECTIONS

adults and children 6 years and over | one 10 mg tablet once daily; do not take more than one 10 mg tablet in 24 hours. A 5 mg product may be appropriate for less severe symptoms.
adults 65 years and over | ask a doctor
children under 6 years of age | ask a doctor
consumers with liver or kidney disease | ask a doctor

STORAGE

- store between 20° to 25°C (68° to 77°F)

Other information

◾Contains no ingredient made from a gluten-containing grain (wheat, barley or rye).

Inactive ingredients

colloidal silicon dioxide, croscarmellose sodium, hypromellose, lactose monohydrate, magnesium stearate, microcrystalline cellulose, polyethylene glycol, titanium dioxide.